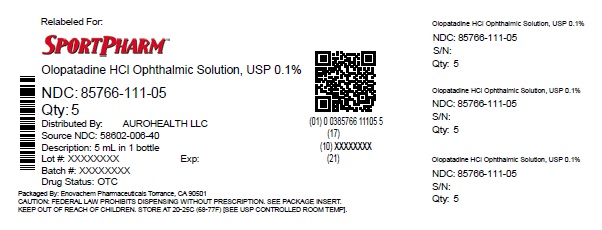 DRUG LABEL: OLOPATADINE HYDROCHLORIDE
NDC: 85766-111 | Form: SOLUTION
Manufacturer: Sportpharm, Inc. dba Sportpharm
Category: otc | Type: HUMAN OTC DRUG LABEL
Date: 20251109

ACTIVE INGREDIENTS: OLOPATADINE HYDROCHLORIDE 1 mg/1 mL
INACTIVE INGREDIENTS: BENZALKONIUM CHLORIDE; SODIUM PHOSPHATE, DIBASIC, UNSPECIFIED FORM; SODIUM CHLORIDE; HYDROCHLORIC ACID; SODIUM HYDROXIDE; WATER

Drug Facts

Active ingredient
Olopatadine (0.1%).
(equivalent to olopatadine hydrochloride, USP 0.111%)

Purpose

Antihistamine and Redness Reliever

Uses

temporarily relieves itchy and red eyes due to pollen, ragweed, grass, animal hair and dander

Warnings

For external use only

Do not use

- if solution changes color or becomes cloudy
- if you are sensitive to any ingredient in this product
- to treat contact lens related irritation

When using this product

- do not touch tip of container to any surface to avoid contamination
- remove contact lenses before use
- wait at least 10 minutes before reinserting contact lenses after use
- do not wear a contact lens if your eye is red

Stop use and ask a doctor ifyou experience:

- eye pain
- changes in vision
- increased redness of the eye
- itching worsens or lasts for more than 72 hours

Keep Out of Reach of Children.

If swallowed, get medical help or contact a Poison Control Center (1-800-222-1222) right away.

Directions

- adults and children 2 years of age and older:
  - put 1 drop in the affected eye(s) twice daily, every 6 to 8 hours, no more than twice per day
  - if using other ophthalmic products while using this product, wait at least 5 minutes between each product
  - replace cap after each use
- children under 2 years of age:

consult a doctor

Other information

- only for use in the eye
- store between 4° to 25°C (39° to 77°F)

Inactive ingredients

benzalkonium chloride 0.01%, dibasic sodium phosphate, hydrochloric acid/sodium hydroxide (adjust pH), sodium chloride and water for injection

Questions?

✆1-855-274-4122

Distributed by:

Sportpharm

2237 N Commerce Parkway,

STE 1, Weston, Florida-33326

Relabeled by:

Enovachem PHARMACEUTICALS

Torrance, CA 90501